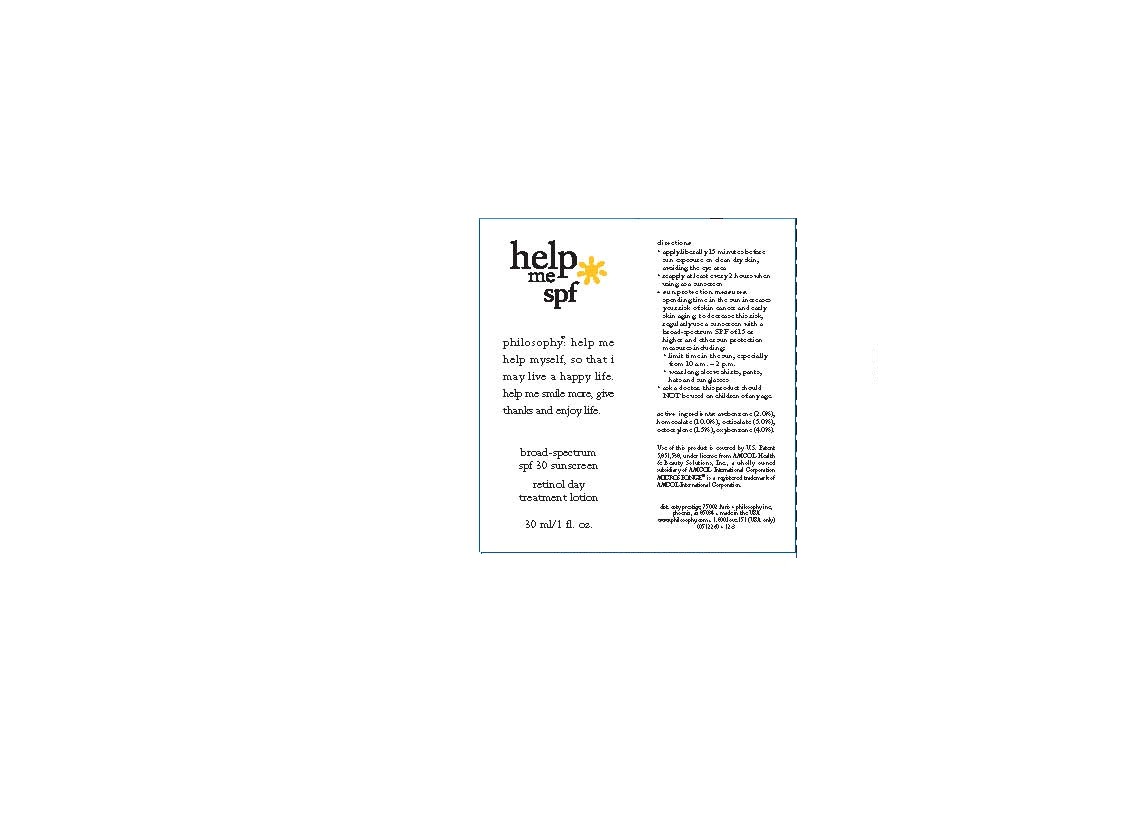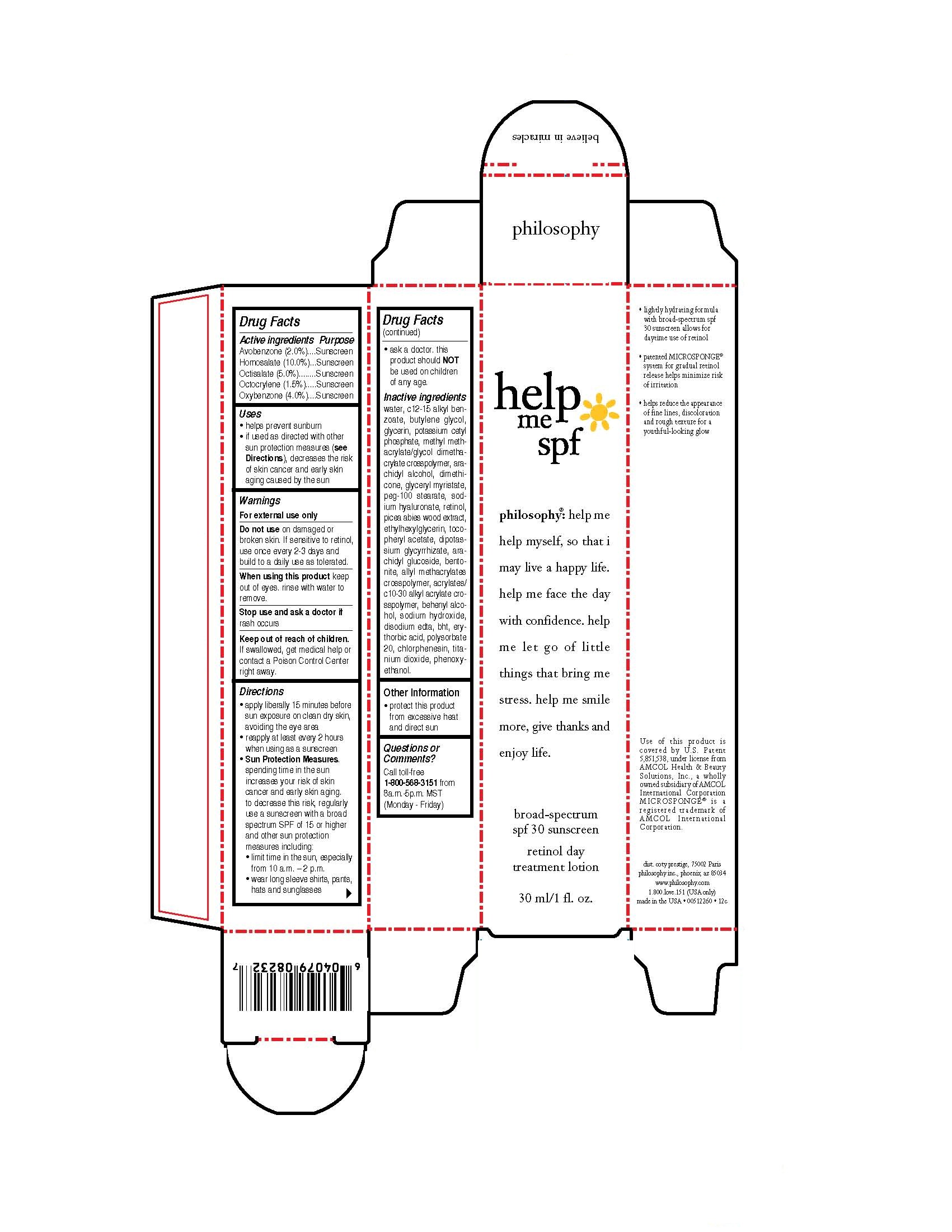 DRUG LABEL: help me
NDC: 50184-1000 | Form: LIQUID
Manufacturer: Philosophy Inc.
Category: otc | Type: HUMAN OTC DRUG LABEL
Date: 20120411

ACTIVE INGREDIENTS: Avobenzone 0.6 mL/30 mL; Homosalate 3 mL/30 mL; Octisalate 1.5 mL/30 mL; Octocrylene 0.45 mL/30 mL; Oxybenzone 1.2 mL/30 mL
INACTIVE INGREDIENTS: Water; ALKYL (C12-15) BENZOATE; butylene glycol; glycerin; potassium cetyl phosphate; arachidyl alcohol; dimethicone; glyceryl myristate; peg-100 stearate; HYALURONATE SODIUM; retinol; PICEA ABIES FLOWER BUD ; ethylhexylglycerin; ALPHA-TOCOPHEROL ACETATE; GLYCYRRHIZINATE DIPOTASSIUM; arachidyl glucoside; bentonite;  DOCOSANOL; sodium hydroxide; EDETATE DISODIUM; BUTYLATED HYDROXYTOLUENE; erythorbic acid; polysorbate 20; chlorphenesin; titanium dioxide; phenoxyethanol 

DRUG FACTS

ACTIVE INGREDIENT

Avobenzone 2.0%

Homosalate 10.0%

Octisalate 5.0%

Octocrylene 1.5%

Oxybenzone 4.0%

PURPOSE

Avobenzone: Sunscreen

Homosalate: Sunscreen

Octisalate: Sunscreen

Octocrylene: Sunscreen

Oxybenzone: Sunscreen

Keep out of reach of children. If swallowed, get medical help or contact a Poison Control Center right away.

INDICATIONS AND USAGE

- Helps prevent sunburn
- If used as directed with other sun protection measures (see Directions), decreases the risk of skin cancer and early skin aging caused by the sun.

WARNINGS

For external use only.

Do not use on damaged or broken skin. If sensitive to retinol, use once every 2-3 days build to a daily use as tolerated.

When using this product keep out of eyes, rinse with water to remove.

Stop use and ask a doctor if rash occurs.

DOSAGE AND ADMINISTRATION

- apply liberally 15 minutes before sun exposure on clean dry skin, avoiding the eye area
- reapply at least every 2 hours when using as a sunscreen
- Sun Protection Measures. spending time in the sun increases your risk of skin cancer and early skin aging. to decrease this risk, regularly use a sunscreen with a broad spectrum SPF of 15 or higher and other sun protection measures including:

limit time int he sun, especially from 10 a.m.-2 p.m.
wear long sleeve shirts, pants, hats and sunglasses
ask a doctor. this product should NOT be used on children of any age.

INACTIVE INGREDIENT

water, c12-15 alkyl benzoate, butylene glycol, glycerin, potassium cetyl phosphate, methyl methacrylate/glycol dimethacrylate crosspolymer, arachidyl alcohol, dimethicone, glyceryl myristate, peg-100 stearate, sodium hyaluronate, retinol, picea abies wood extract, ethylhexylglycerin, tocopheryl acetate, dipotassium glycyrrhizate, arachidyl glucoside, bentonite, allyl methacrylates crosspolymer, acrylates/c10-30 alkyl acrylate crosspolymer, behenyl alcohol, sodium hydroxide, disodium edta, bht, erythorbic acid, polysorbate 20, chlorphenesin, titanium dioxide, phenoxyethanol.